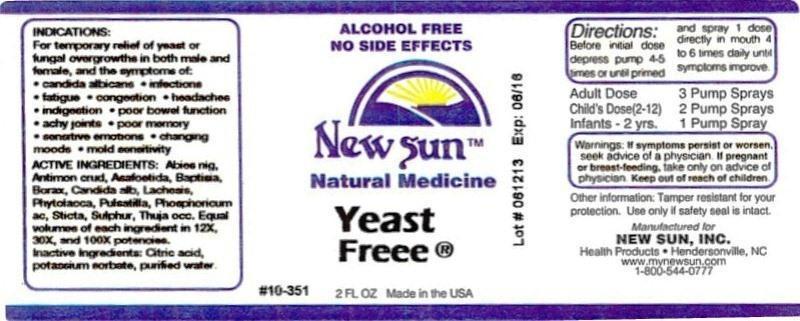 DRUG LABEL: Yeast Freee
NDC: 66579-0061 | Form: LIQUID
Manufacturer: New Sun Inc.
Category: homeopathic | Type: HUMAN OTC DRUG LABEL
Date: 20140829

ACTIVE INGREDIENTS: PICEA MARIANA RESIN 12 [hp_X]/59 mL; ANTIMONY TRISULFIDE 12 [hp_X]/59 mL; ASAFETIDA 12 [hp_X]/59 mL; BAPTISIA TINCTORIA ROOT 12 [hp_X]/59 mL; SODIUM BORATE 12 [hp_X]/59 mL; CANDIDA ALBICANS 12 [hp_X]/59 mL; LACHESIS MUTA VENOM 12 [hp_X]/59 mL; PHYTOLACCA AMERICANA ROOT 12 [hp_X]/59 mL; PHOSPHORIC ACID 12 [hp_X]/59 mL; PULSATILLA VULGARIS 12 [hp_X]/59 mL; LOBARIA PULMONARIA 12 [hp_X]/59 mL; SULFUR 12 [hp_X]/59 mL; THUJA OCCIDENTALIS LEAFY TWIG 12 [hp_X]/59 mL
INACTIVE INGREDIENTS: CITRIC ACID MONOHYDRATE; POTASSIUM SORBATE; WATER

Yeast Freee

DOSAGE AND ADMINISTRATION

Directions: Before initial dose depress pump 4-5 times or until primed and spray 1 dose directly in mouth 4 to 6 times daily until symptoms improve.

Adult Dose: 3 Pump Sprays

Child's Dose (2-12): 2 Pump Sprays

Infants - 2 yrs. 1 Pump Spray

WARNINGS

Warnings: If symptoms persist or worsen, seek advice of physician. If pregnant or breast-feeding, take only on advice of physician.

Keep out of reach of children.

Other information: Tamper resistant for your protection. Use only if safety seal is intact.

PURPOSE

Indications: For temporary relief of yeast or fungal overgrowths in both male and female, and the symptoms of: candida albicans, infections, fatigue, congestion, headaches, indigestion, poor bowel function, achy joints, poor memory, sensitive emotions, changing moods, mold sensitivity.

ACTIVE INGREDIENT

Active Ingredients: Abies nigra, Antimonium crudum, Asafoetida, Baptisia tinctoria, Borax, Candida albicans, Lachesis mutus, Phytolacca decandra, Phosphoricum acidum, Pulsatilla, Sticta pulmonaria, Sulphur, Thuja occidentalis. Equal volumes of each ingredient in 12X, 30X, 100X potencies.

Inactive Ingredient: Citric acid, potassium sorbate, purified water.

INDICATIONS AND USAGE

Indications: For temporary relief of yeast or fungal overgrowths in both male and female, and the symptoms of:

- candida albicans
- infections
- fatigue
- congestion
- headaches
- indigestion
- poor bowel function
- achy joints
- poor memory
- sensitive emotions
- changing moods
- mold sensitivity